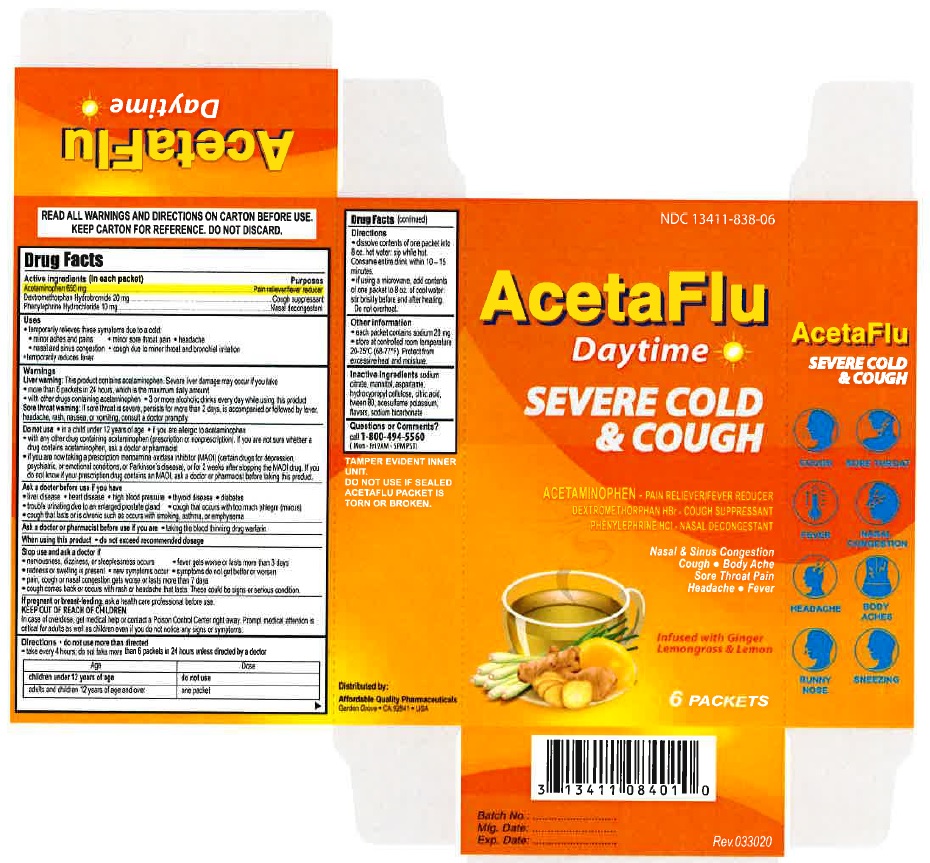 DRUG LABEL: AcetaFlu DayTime
NDC: 13411-838 | Form: POWDER
Manufacturer: Advanced Pharmaceutical Services, Inc. Dba Affordable Quality Pharmaceuticals
Category: otc | Type: HUMAN OTC DRUG LABEL
Date: 20200326

ACTIVE INGREDIENTS: ACETAMINOPHEN 650 mg/2 g; DEXTROMETHORPHAN HYDROBROMIDE 25 mg/2 g; PHENYLEPHRINE HYDROCHLORIDE 10 mg/2 g
INACTIVE INGREDIENTS: SODIUM CITRATE; MANNITOL; ASPARTAME; HYDROXYPROPYL CELLULOSE, UNSPECIFIED; CITRIC ACID MONOHYDRATE; ANHYDROUS CITRIC ACID; POLYSORBATE 80; ACESULFAME POTASSIUM; SODIUM BICARBONATE

Active ingredients (in each packet) Purposes

Acetaminophen 650 mg.............................................................................Pain reliever/fever reducer
Dextromethorphan hydrobromide 20 mg.....................................................Cough suppressant
Phenylephrine hydrochloride 10 mg............................................................Nasal decongestant

Uses
• temporarily relieves these symptoms due to a cold:
• minor aches and pains • minor sore throat pain • headache
• nasal and sinus congestion • cough due to minor throat and bronchial irritation
•temporarily reduces fever

Warnings
Liver warning: This product contains acetaminophen. Severe liver damage may occur if you take
• more than 6 packets in 24 hours, which is the maximum daily amount
• with other drugs containing acetaminophen • 3 or more alcoholic drinks every day while using this product
Sore throat warning: If sore throat is severe, persists for more than 2 days, is accompanied or followed by fever,
headache, rash, nausea, or vomiting, consult a doctor promptly.

Do not use • in a child under 12 years of age • if you are allergic to acetaminophen
• with any other drug containing acetaminophen (prescription or nonprescription). If you are not sure whether a drug contains acetaminophen, ask a doctor or pharmacist
• if you are now taking a prescription monoamine oxidase inhibitor (MAOI) (certain drugs for depression, psychiatric, or emotional conditions, or Parkinson’s disease), or for 2 weeks after stopping the MAOI drug. If you do not know if your prescription drug contains an MAOI, ask a doctor or pharmacist before taking this product.

Ask a doctor before use if you have
• liver disease • heart disease • high blood pressure • thyroid disease • diabetes
• trouble urinating due to an enlarged prostate gland • cough that occurs with too much phlegm (mucus)
• cough that lasts or is chronic such as occurs with smoking, asthma, or emphysema

Ask a doctor or pharmacist before use if you are • taking the blood thinning drug warfarin

When using this product • do not exceed recommended dosage

Stop use and ask a doctor if
• nervousness, dizziness, or sleeplessness occurs • fever gets worse or lasts more than 3 days
• redness or swelling is present • new symptoms occur • symptoms do not get better or worsen
• pain, cough or nasal congestion gets worse or lasts more than 7 days
• cough comes back or occurs with fever, rash or headache that lasts. These could be signs or serious condition.

If pregnant or breast-feeding, ask a health care professional before use.

KEEP OUT OF REACH OF CHILDREN.
In case of overdose, get medical help or contact a Poison Control Center right away. Prompt medical attention is
critical for adults as well as children even if you do not notice any signs or symptoms.

Directions

• do not use more than directed
• take every 4 hours; do not take more than 6 packets in 24 hours unless directed by a doctor

Age Dose

children under 4 years of age do not use
children 4 to under 12 years of age do not use unless directed by a doctor
adults and children 12 years of age and over one packet

• dissolve contents of one packet into 8 oz. hot water: sip while hot. Consume entire drink within 10 – 15 minutes.

• if using a microwave, add contents of one packet to 8 oz. of cool water: stir briskly before and after heating.
Do not overheat.

Other information
• each packet contains: sodium 20 mg
• store at controlled room temperature 20-25ºC (68-77ºF). Protect from excessive heat and moisture.

Inactive ingredients

sodium citrate, mannitol, aspartame, hydroxypropyl cellulose, citric acid, tween 80, acesulfame potassium, flavors, sodium bicarbonate